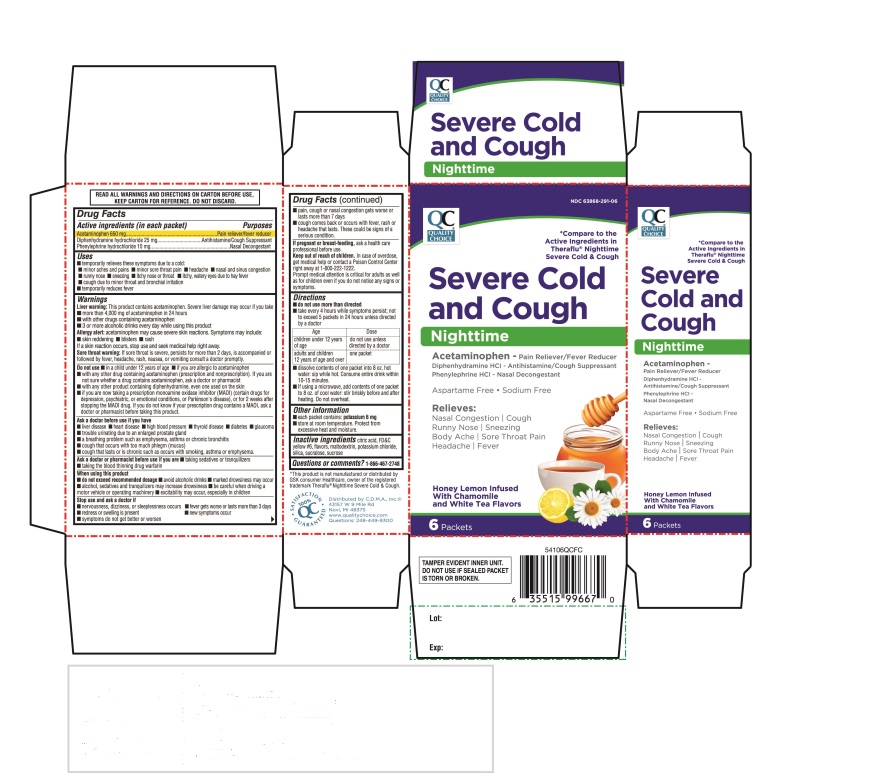 DRUG LABEL: Quality Choice Severe Cold and Cough Nighttime
NDC: 63868-291 | Form: POWDER, FOR SOLUTION
Manufacturer: Chain Drug Manufacturing Assn
Category: otc | Type: HUMAN OTC DRUG LABEL
Date: 20251204

ACTIVE INGREDIENTS: ACETAMINOPHEN 650 mg/1 1; DIPHENHYDRAMINE HYDROCHLORIDE 25 mg/1 1; PHENYLEPHRINE HYDROCHLORIDE 10 mg/1 1
INACTIVE INGREDIENTS: ANHYDROUS CITRIC ACID; FD&C YELLOW NO. 6; MALTODEXTRIN; POTASSIUM CHLORIDE; SILICON DIOXIDE; SUCRALOSE; SUCROSE

QC Quality Choice Severe Cold and Cough Nighttime 6 Packets

Active ingredients (in each packet)

Acetaminophen, 650 mg

Diphenhydramine hydrochloride 25 mg

Phenylephrine hydrochloride 10 mg

Purposes

Pain reliever / fever reducer

Antihistamine / Cough Suppressant

Nasal Decongestant

Uses

- temporarily relieves these symptoms due to a cold:
  - minor aches and pains
  - minor sore throat pain
  - headache
  - nasal and sinus congestion
  - runny nose
  - sneezing
  - itchy nose or throat
  - itchy, watery eyes due to hay fever
  - cough due to minor throat and bronchial irritation
- temporarily reduces fever

Warnings

Liver warning:This product contains acetaminophen. Severe liver damage may occur if you take

- more than 4,000 mg of acetaminophen in 24 hours
- with other drugs containing acetaminophen
- 3 or more alcoholic drinks every day while using this product

Allergy alert:acetaminophen may cause severe skin reactions, Symptoms may include:

- skin reddening
- blisters
- rash

If a skin reaction occurs, stop use and seek medical help right away

Sore throat warning:If sore throat is severe, persists for more than 2 days, is accompanied or followed by fever, headache, rash, nausea, or vomiting consult a doctor promptly.

Do not use

- in a child under 12 years of age
- if you are allergic to acetaminophen
- with any other drug containing acetaminophen (prescription or nonprescription). If you are not sure whether a drug contains acetaminophen, ask a doctor or a pharmacist.
- with any other product containing diphenhydramine, even one used on the skin
- if you are now taking a prescription monoamine oxidase inhibitor (MAOI) (certain drugs for depression, psychiatric, or emotional conditions, or Parkinson's disease), or for 2 weeks after stopping the MAOI drug. If you do not know if your prescription drug contains a MAOI, ask a doctor or pharmacist before taking this product.

Ask a doctor before use if you have

- liver disease
- heart disease
- high blood pressure
- thyroid disease
- diabetes
- glaucoma
- trouble urinating due to an enlarged prostate gland
- a breathing problem such as emphysema, asthma or chronic bronchitis
- cough that occurs with too much phlegm (mucus)
- cough that lasts or is chronic such as occurs with smoking, asthma or emphysema

Ask a doctor or pharmacist before use if you are

- taking sedatives or tranquilizers
- taking the blood thinning drug warfarin

When using this product

- do not exceed recommended dosage
- avoid alcoholic drinks
- marked drowsiness may occur
- alcohol, sedatives and tranquilizers may increase drowsiness
- be careful when driving a motor vehicle or operating machinery
- excitability may occur, especially in children

Stop use and ask a doctor if

- nervousness, dizziness, or sleeplessness occurs
- fever gets worse or lasts more than 3 days
- redness or swelling is present
- new symptoms occur
- symptoms do not get better or worsen
- pain, cough or nasal congestion gets worse or lasts more than 7 days
- cough comes back or occurs with fever, rash or headache that lasts. There could be signs of a serious condition.

If pregnant or breast- feeding,

ask a health care professional before use.

Keep out of reach of children.

In case of overdose, get medical help or contact a Poison Control Center right away at 1-800-222-1222. Prompt medical attention is critical for adults as well as for children even if you do not notice any signs or symptoms.

Directions

- do not use more than directed
- take every 4 hours while symptoms persist, not to exceed 5 packets in 24 hours unless directed by a doctor

Age | Dose
children under 12 years of age | do not use unless directed by a doctor
adults and children 12 years of age and over | one packet

- dissolve contents of one packet into 8 oz. hot water: sip while hot. Consume entire drink within 10 - 15 minutes.
- if using a microwave, add contents of one packet to 8 oz. of cool water: stir briskly before and after heating, Do not overheat.

Other information

- each packet contains: potassium 6 mg
- store at room temperature. Protect from excessive heat and moisture.

Inactive ingredients

citric acid, FD& C yellow#6, flavors, maltodextrin, potassium chloride, silica, sucralose, sucrose,

Questions or comments?

1-866-467-2748

Additional Information Listed On Other Panels

QC Quality Choice

*Compare to the Active Ingredients in Theraflu® Nighttime Severe Cold &Cough

Severe Cold & Cough

Nighttime

Acetaminophen -Pain Reliever/ Fever Reducer

Diphenhydramine HCl - Antihistamine/ Cough Suppressant

Phenylephrine HCl - Nasal Decongestant

Aspartame Free● Sodium Free

- Relieves :
- Nasal Congestion ǀ Cough ǀ Runny Nose ǀ Sneezing ǀ Body Ache ǀ Sore Throat Pain ǀ Headache ǀ Fever.

Honey Lemon Infused with Chamomile and White Tea Flavors

6 Packets

READ ALL WARNINGS AND DIRECTIONS ON CARTON BEFORE USE, KEEP CARTON FOR REFERENCE, DO NOT DISCARD,

TAMPER EVIDENT INNER UNIT: DO NOT USE IF SEALED PACKET IS TORN OR BROKEN.

Distributed by: C.D.M.A., Inc ©

43157 W. 9 Mile Rd

Novi, MI 48375

www.qualitychoice.com

Questions: 248-449-9300

*This product is not manufactured or distributed by GSK Consumer Healthcare, owner of the registered trademark Theraflu®Nighttime Severe Cold & Cough.